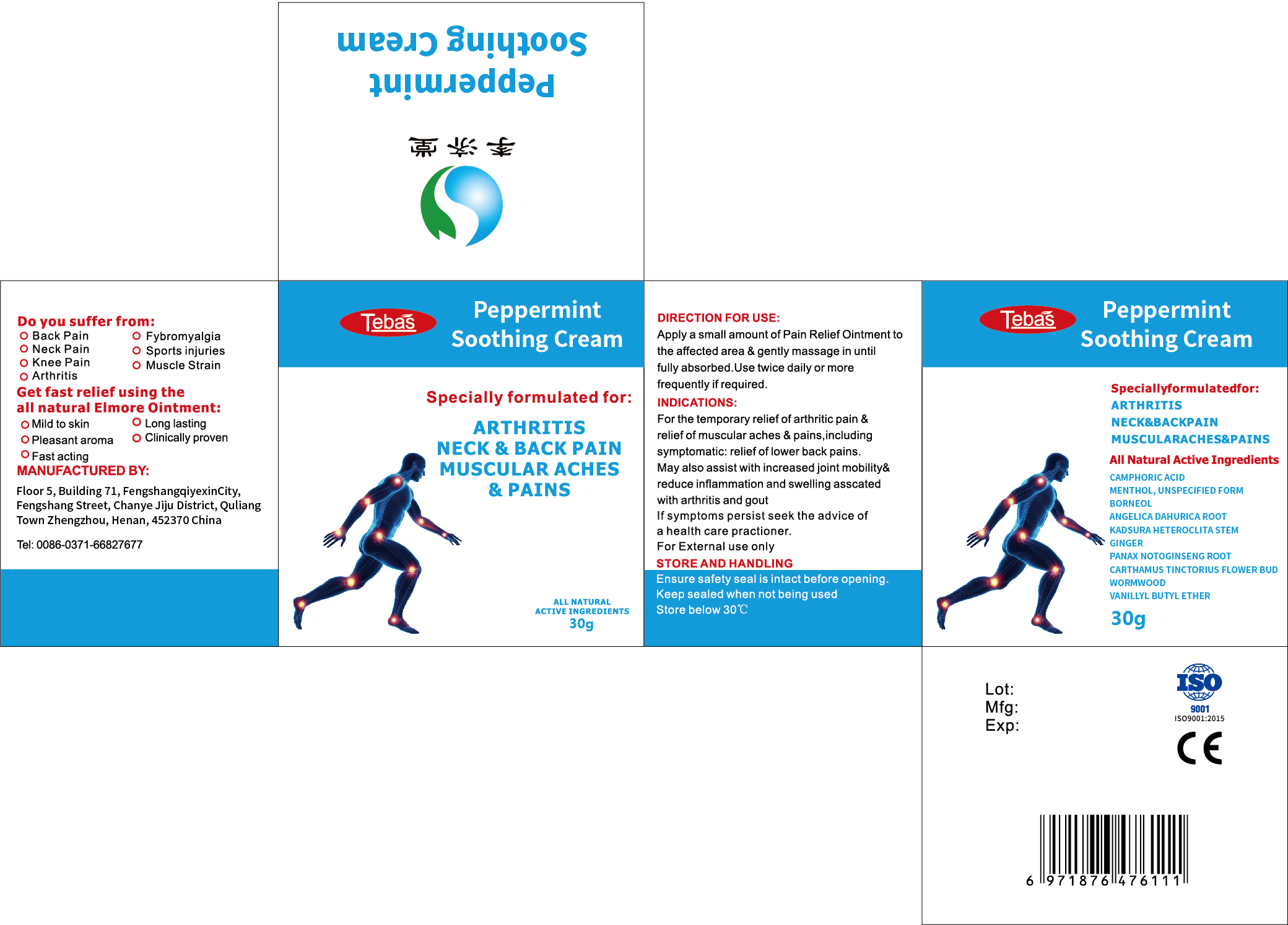 DRUG LABEL: Peppermint soothing cream
NDC: 85305-001 | Form: PASTE
Manufacturer: Henan Lijitang Medical Technology Co., Ltd.
Category: otc | Type: HUMAN OTC DRUG LABEL
Date: 20250303

ACTIVE INGREDIENTS: CAMPHORIC ACID 3.5 g/100 g; MENTHOL, UNSPECIFIED FORM 2 g/100 g; BORNEOL 1 g/100 g
INACTIVE INGREDIENTS: KADSURA HETEROCLITA STEM; ANGELICA DAHURICA ROOT; PANAX NOTOGINSENG ROOT; WORMWOOD; VANILLYL BUTYL ETHER; CARTHAMUS TINCTORIUS FLOWER BUD; GINGER

Peppermint soothing cream

ACTIVE INGREDIENT

CAMPHORIC ACID 3.5%
MENTHOL, UNSPECIFIED FORM 2%
BORNEOL 1%

PURPOSE

pain relief

INDICATIONS AND USAGE

Specially formulated for: ARTHRITISNECK & BACK PAINMUSCULAR ACHES& PAINS

WARNINGS

For External use only

not be administered to pregnant women

KEEP OUT OF REACH OF CHILDREN SECTION

DOSAGE AND ADMINISTRATION

Apply a small amount of Pain Relief Ointment tothe affected area & gently massage in untilfully absorbed.Use twice daily or morefrequently if required.

INACTIVE INGREDIENT

ANGELICA DAHURICA ROOT
KADSURA HETEROCLITA STEM
GINGER
PANAX NOTOGINSENG ROOT
CARTHAMUS TINCTORIUS FLOWER BUD
WORMWOOD
VANILLYL BUTYL ETHER